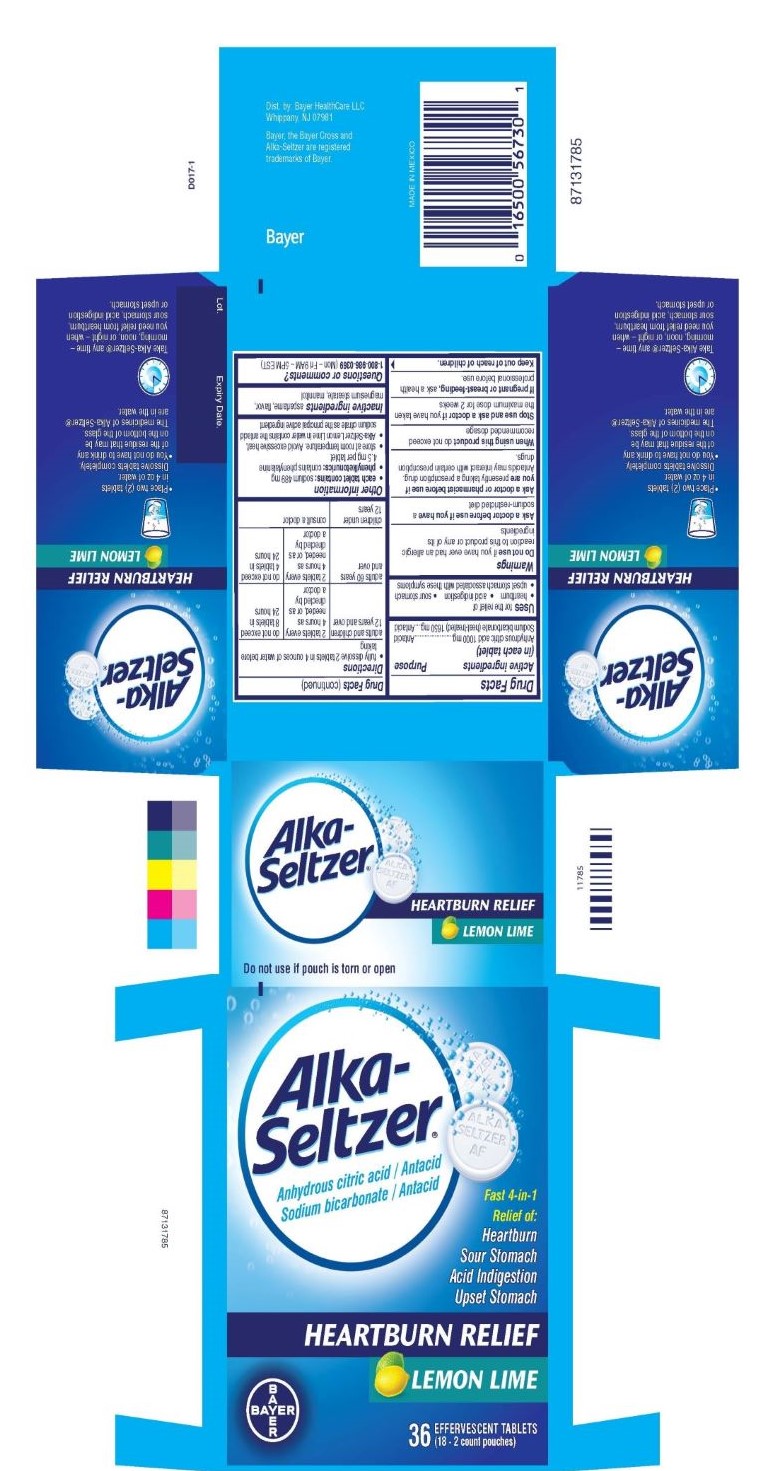 DRUG LABEL: Alka-Seltzer Heartburn Relief Lemon Lime
NDC: 0280-0083 | Form: TABLET, EFFERVESCENT
Manufacturer: Bayer Healthcare LLC
Category: otc | Type: HUMAN OTC DRUG LABEL
Date: 20250401

ACTIVE INGREDIENTS: SODIUM BICARBONATE 1650 mg/1 1; CITRIC ACID MONOHYDRATE 1000 mg/1 1
INACTIVE INGREDIENTS: ASPARTAME; MAGNESIUM STEARATE; MANNITOL

Alka-Seltzer Heartburn Relief Lemon Lime

Drug Facts

ACTIVE INGREDIENT

Anhydrous citric acid 1000 mg
Sodium bicarbonate (heat-treated) 1650 mg

PURPOSE

Antacid
Antacid

INDICATIONS AND USAGE

Uses for the relief of

- heartburn
- acid indigestion
- sour stomach
- upset stomach associated with these symptoms

Warnings

Do not use if you have ever had an allergic reaction to this product or any of its ingredients

Ask a doctor before use if you have a sodium-restricted diet

Ask a doctor or pharmacist before use if you are presently taking a prescription drug. Antacids may interact with certain prescription drugs.

When using this product do not exceed recommended dosage

Stop use and ask a doctor if you have taken the maximum dose for 2 weeks

PREGNANCY OR BREAST FEEDING

If pregnant or breast-feeding, ask a health professional before use.

Keep out of reach of children.

Directions

● fully dissolve 2 tablets in 4 ounces of water before taking

adults and children 12 years and over | 2 tablets every 4 hours as needed, or as directed by a doctor | do not exceed 8 tablets in 24 hours
adults 60 years and over | 2 tablets every 4 hours as needed, or as directed by a doctor | do not exceed 4 tablets in 24 hours
children under 12 years | consult a doctor

Other information

● each tablet contains: sodium 489 mg
● phenylketonurics: contains phenylalanine 4.5 mg per tablet
● store at room temperature. Avoid excessive heat.
● Alka-Seltzer Lemon Lime in water contains the antacid sodium citrate as the principal active ingredient

Inactive ingredients

aspartame, flavor, magnesium stearate, mannitol

Questions or comments? 1-800-986-0369 (Mon – Fri 9AM – 5PM EST)

Dist. by: Bayer HealthCare LLC

Whippany, NJ 07981

PACKAGE LABEL

ALKA-SELTZER

Fast 4-in-1

Relief of:

Heartburn

Sour Stomach

Acid Indigestion

Upset Stomach

HEARTBURN RELIEF

LEMON LIME

36 EFFERVESCENT TABLETS

(18 - 2 count pouches)